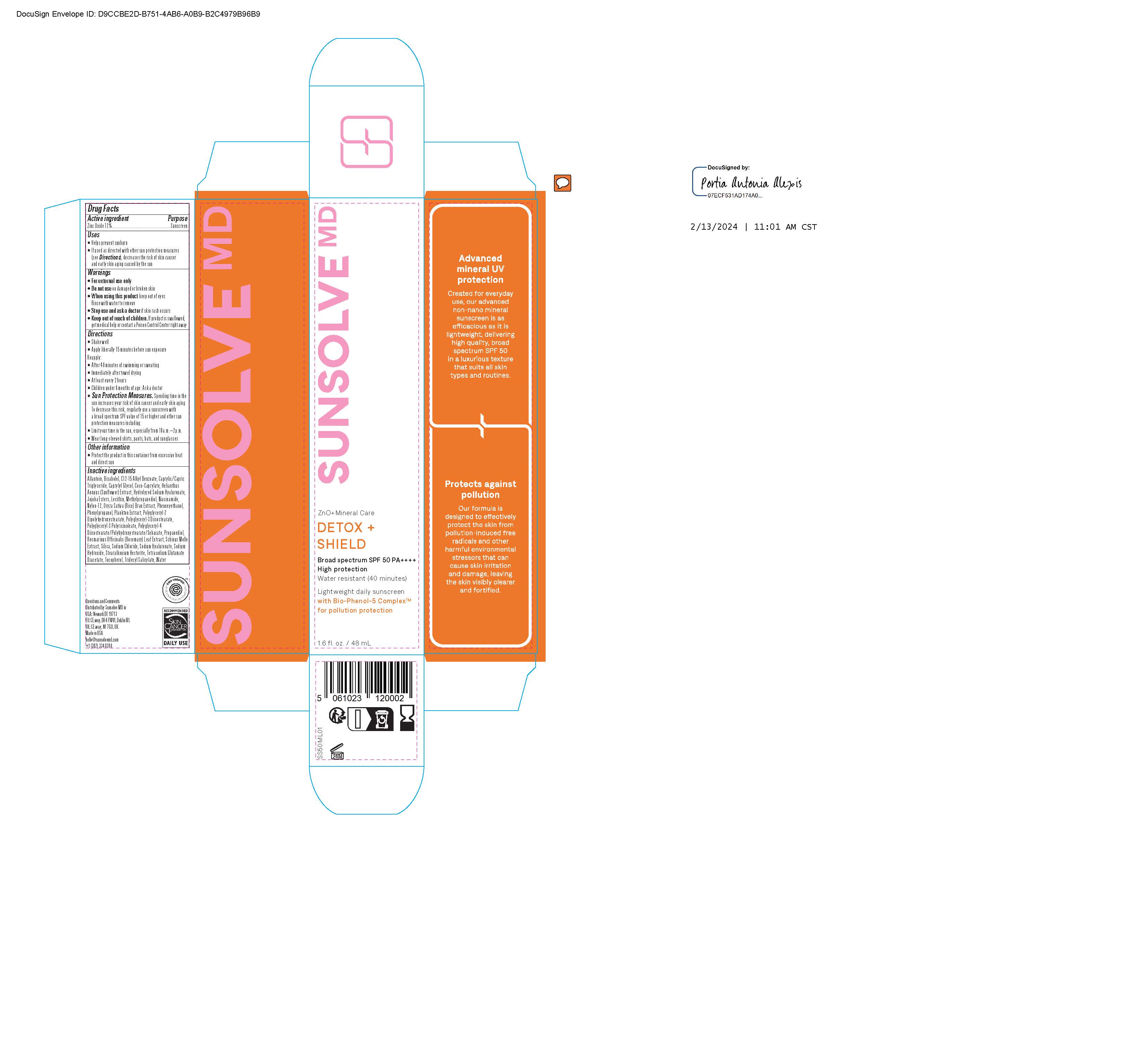 DRUG LABEL: Sunsolve MD Detox and Shield
NDC: 84878-998 | Form: LOTION
Manufacturer: Sunsolve MD Inc
Category: otc | Type: HUMAN OTC DRUG LABEL
Date: 20251114

ACTIVE INGREDIENTS: ZINC OXIDE 132 mg/1 mL
INACTIVE INGREDIENTS: JOJOBA OIL; SCHINUS MOLLE OIL; ORYZA SATIVA WHOLE; TRIDECYL SALICYLATE; SILICON DIOXIDE; TOCOPHEROL; CAPRYLYL GLYCOL; COCO-CAPRYLATE; NYLON-12; PHENYLPROPANOL; HELIANTHUS ANNUUS FLOWERING TOP; LECITHIN, SOYBEAN; METHYLPROPANEDIOL; POLYGLYCERYL-2 DIPOLYHYDROXYSTEARATE; ALLANTOIN; ALKYL (C12-15) BENZOATE; ROSMARINUS OFFICINALIS FLOWER; .ALPHA.-BISABOLOL, (+)-; SODIUM HYDROXIDE; WATER; NIACINAMIDE; PROPANEDIOL; TETRASODIUM GLUTAMATE DIACETATE; SODIUM CHLORIDE; POLYGLYCERYL-4 DIISOSTEARATE/POLYHYDROXYSTEARATE/SEBACATE; POLYGLYCERYL-3 DIISOSTEARATE; STEARALKONIUM HECTORITE; CAPRYLIC/CAPRIC TRIGLYCERIDE; PHENOXYETHANOL

Sunsolve MD Detox and Shield